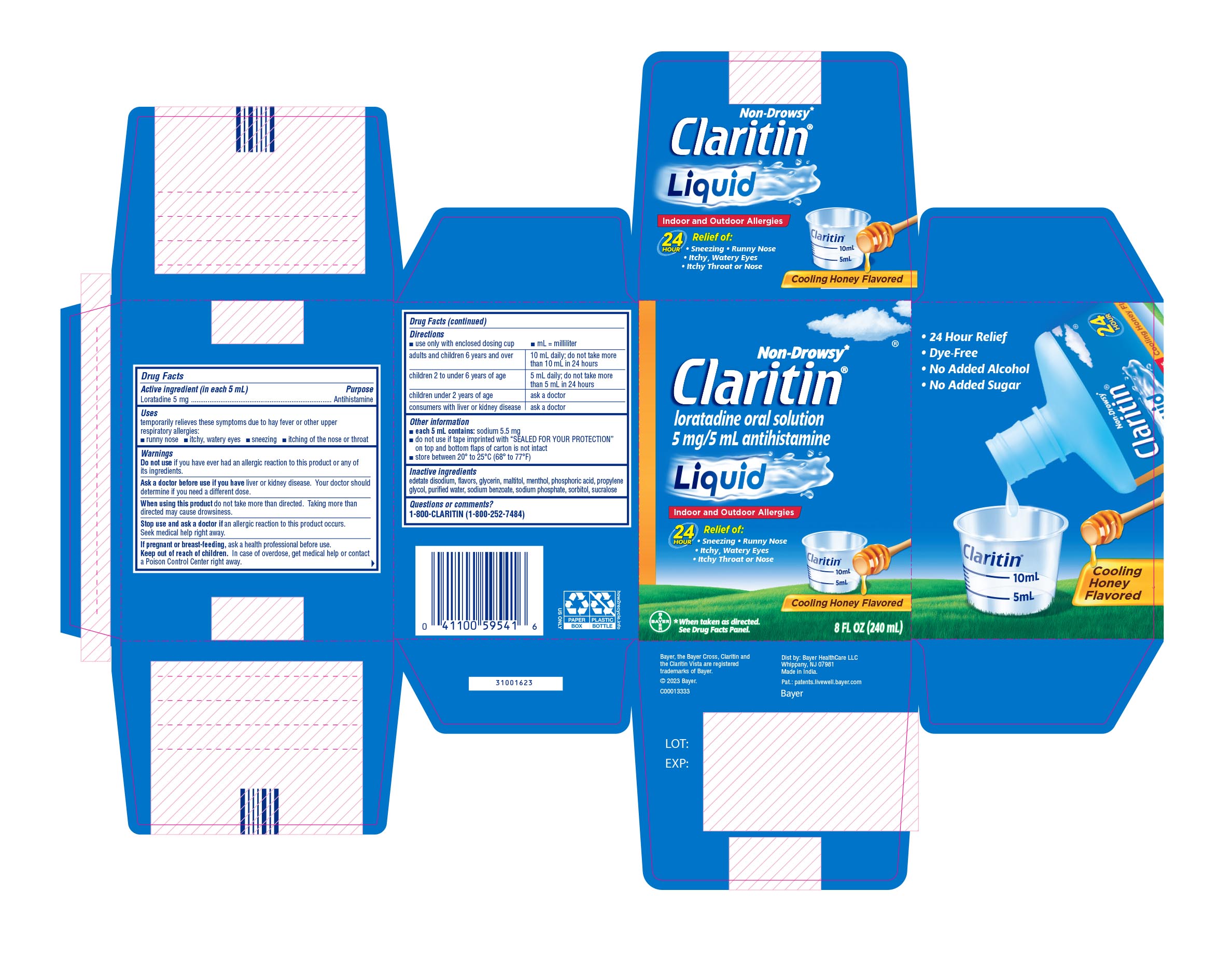 DRUG LABEL: Claritin
NDC: 11523-0101 | Form: SOLUTION
Manufacturer: Bayer HealthCare LLC.
Category: otc | Type: HUMAN OTC DRUG LABEL
Date: 20251204

ACTIVE INGREDIENTS: LORATADINE 1 mg/1 mL
INACTIVE INGREDIENTS: EDETATE DISODIUM; SORBITOL; MALTITOL; GLYCERIN; PHOSPHORIC ACID; SUCRALOSE; WATER; SODIUM PHOSPHATE, MONOBASIC; PROPYLENE GLYCOL; SODIUM BENZOATE

Claritin Liquid Cooling Honey UI 1613938

Active ingredient (in each 5 mL teaspoonful)

Loratadine 5 mg

Purpose

Antihistamine

Uses

temporarily relieves these symptoms due to hay fever or other upper respiratory allergies:

- runny nose
- itchy, watery eyes
- sneezing
- itching of the nose or throat

Do not use if you have ever had an allergic reaction to this product or any of its ingredients.

Ask a doctor before use if you have liver or kidney disease. Your doctor should determine if you need a different dose.

When using this product do not take more than directed. Taking more than directed may cause drowsiness.

Stop use and ask a doctor if an allergic reaction to this product occurs. Seek medical help right away.

PREGNANCY OR BREAST FEEDING

If pregnant or breast-feeding, ask a health professional before use.

Keep out of reach of children. In case of overdose, get medical help or contact a Poison Control Center right away.

Directions

- use only with enclosed dosing cup
- mL = milliliter

Adults and children 6 years and over: 10 mL daily, do not take more than 10mL in 24 hours; children 2 to under 6 years of age: 5mL daily, do not take more than 5mL in 24 hours; children under 2 years of age: ask a doctor

Other Information

- each 5 mL contains: sodium 5.5 mg
- do not use if tape imprinted with “SEALED FOR YOUR PROTECTION” on top and bottom flaps of carton is not intact.
- store between 20° and 25°C (68° and 77°F)

INACTIVE INGREDIENT

edetate disodium, flavors, glycerin, maltitol, menthol, phosphoric acid, propylene glycol, purified water, sodium benzoate, sodium phosphate, sorbitol, sucralose

Questions or comments?

1-800-CLARITIN (1-800-252-7484)